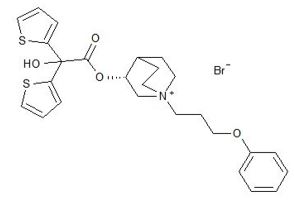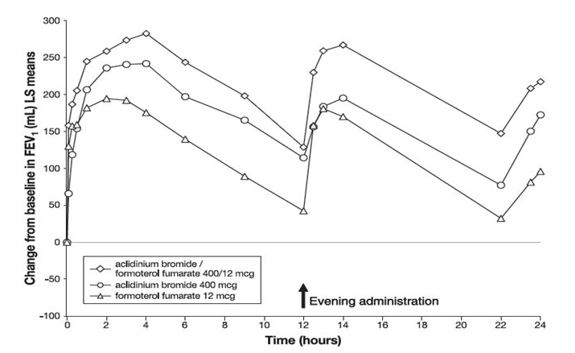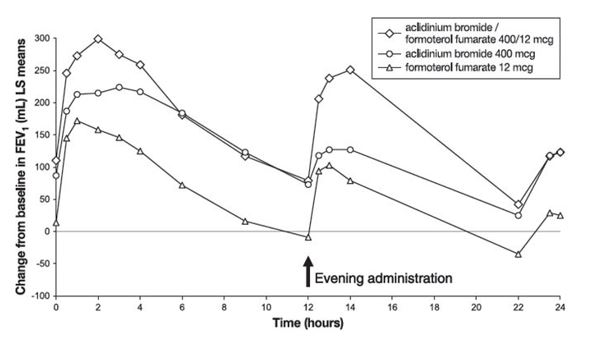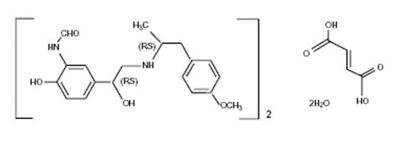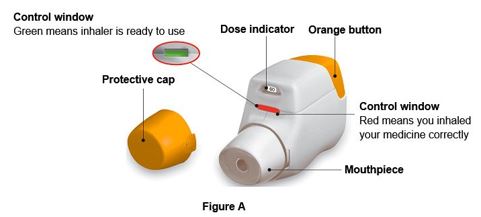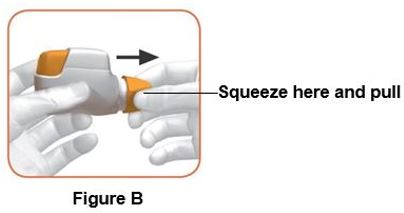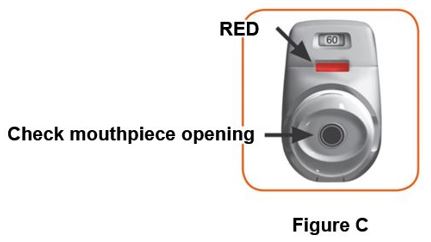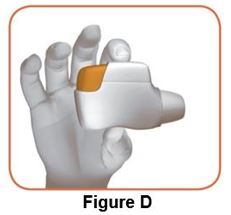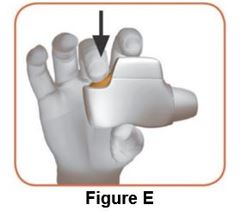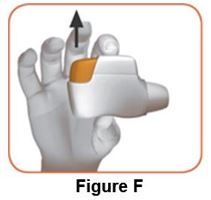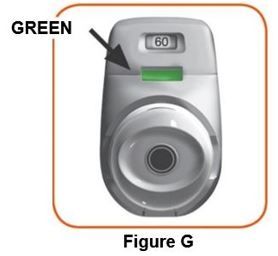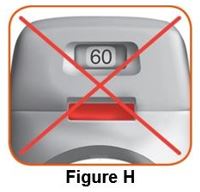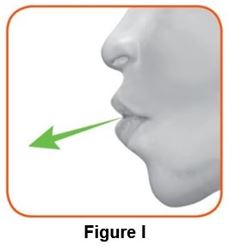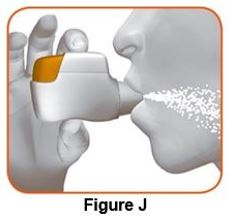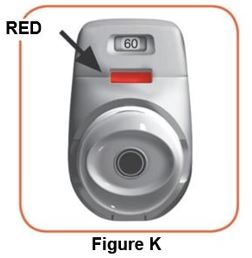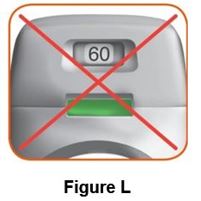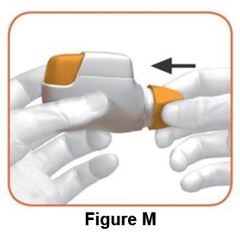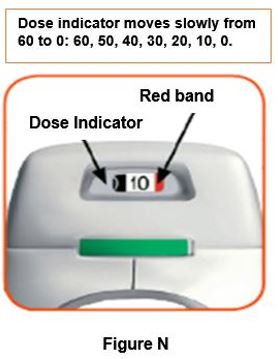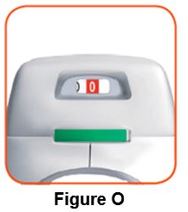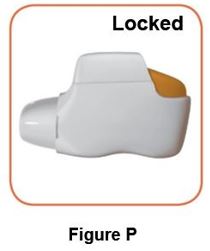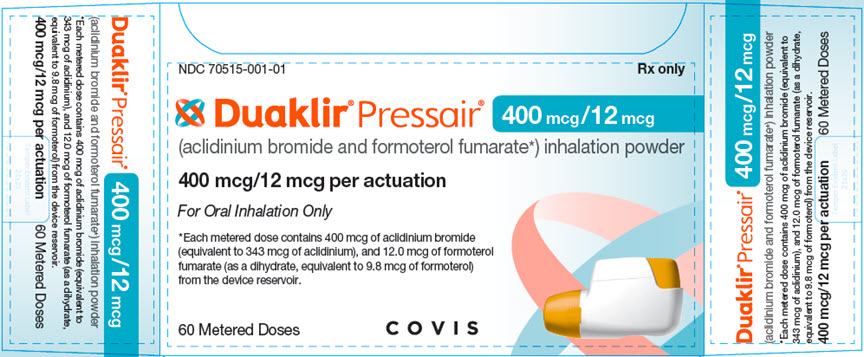 DRUG LABEL: DUAKLIR PRESSAIR
NDC: 70515-001 | Form: POWDER, METERED
Manufacturer: Covis Pharma US, Inc
Category: prescription | Type: HUMAN PRESCRIPTION DRUG LABEL
Date: 20220801

ACTIVE INGREDIENTS: ACLIDINIUM BROMIDE 400 ug/1 1; FORMOTEROL FUMARATE 12 ug/1 1
INACTIVE INGREDIENTS: LACTOSE MONOHYDRATE

HIGHLIGHTS OF PRESCRIBING INFORMATION

These highlights do not include all the information needed to use DUAKLIR PRESSAIR safely and effectively. See full prescribing information for DUAKLIR PRESSAIR.
DUAKLIR® PRESSAIR® (aclidinium bromide and formoterol fumarate) inhalation powder, for oral inhalation
Initial U.S. Approval: 2019

1 INDICATIONS AND USAGE

DUAKLIR PRESSAIR is a combination of aclidinium bromide an anticholinergic, and formoterol fumarate, a long-acting beta2-adrenergic agonist (LABA) indicated for the maintenance treatment of patients with chronic obstructive pulmonary disease (COPD). (1)

Limitations of Use: Not indicated for the relief of acute bronchospasm or for the treatment of asthma. (1, 5.4)

2 DOSAGE AND ADMINISTRATION

- For oral inhalation only. (2)
- 400 mcg/12 mcg, twice daily (once in the morning and once in the evening). (2)

3 DOSAGE FORMS AND STRENGTHS

- Inhalation Powder. (3)
- Breath-actuated multi-dose dry powder inhaler metering 400 mcg of aclidinium bromide and 12 mcg of formoterol fumarate per actuation. (3)

4 CONTRAINDICATIONS

- Use of a long-acting beta2-adrenergic agonist (LABA), including formoterol fumarate, one of the active ingredients in DUAKLIR PRESSAIR, without an inhaled corticosteroid is contraindicated in patients with asthma. (1, 4)
- Hypersensitivity to aclidinium bromide or formoterol fumarate or to any component of this product. (4, 5.5)

5 WARNINGS AND PRECAUTIONS

- Asthma-related death: Long-acting beta2-adrenergic agonists as monotherapy (without an inhaled corticosteroid) for asthma increase the risk of serious asthma-related events. (5.1)
- Do not initiate in acutely deteriorating COPD or to treat acute symptoms. (5.2)
- Do not use in combination with an additional medicine containing a LABA because of risk of overdose. (5.3)
- If paradoxical bronchospasm occurs, discontinue DUAKLIR PRESSAIR and institute alternative therapy. (5.4)
- Use with caution in patients with cardiovascular disorders. (5.6)
- Use with caution in patients with convulsive disorders, thyrotoxicosis, diabetes mellitus and ketoacidosis. (5.7)
- Be alert to hypokalemia and hyperglycemia. (5.8)
- Worsening of narrow-angle glaucoma may occur. Use with caution in patients with narrow-angle glaucoma and instruct patients to contact a physician immediately if symptoms occur. (5.9)
- Worsening urinary retention may occur. Use with caution in patients with prostatic hyperplasia or bladder-neck obstruction and instruct patients to consult a physician immediately if symptoms occur. (5.10)

6 ADVERSE REACTIONS

Most common adverse reactions (incidence ≥ 3% and more common than with placebo) include: upper respiratory tract infection, headache and, back pain. (6.1)

To report SUSPECTED ADVERSE REACTIONS, contact Covis Pharma at 1-877-411-2510 or FDA at 1-800-FDA-1088 or www.fda.gov/medwatch.

7 DRUG INTERACTIONS

- Use of other adrenergic by any route may potentiate the effect of DUAKLIR PRESSAIR. Use with caution. (5.3, 7.1)
- Xanthine derivatives, steroids, diuretics or non-potassium sparing diuretics may potentiate hypokalemia or ECG changes. Use with caution. (7.2, 7.3)
- Diuretics: Use with caution. Electrocardiographic changes and/or hypokalemia associated with non-potassium sparing diuretics may worsen with concomitant beta2-agonists. (7.3)
- Monoamine oxidase inhibitors and tricyclic antidepressants: Use with extreme caution. May potentiate effect of formoterol fumarate on cardiovascular system. (7.4)
- Beta-blockers: Use with caution and only when medically necessary. (7.5)
- Anticholinergics: May interact additively with concomitantly used anticholinergic medications. Avoid administrations of DUAKLIR PRESSAIR with other anticholinergic-containing drugs. (7.6)

FULL PRESCRIBING INFORMATION

1 INDICATIONS AND USAGE

DUAKLIR PRESSAIR is a combination of aclidinium bromide (an anticholinergic) and formoterol fumarate (a LABA) indicated for the maintenance treatment of patients with chronic obstructive pulmonary disease (COPD).

Limitations of Use: DUAKLIR PRESSAIR is not indicated for the relief of acute bronchospasm or for the treatment of asthma [see Warnings and Precautions (5.1, 5.4)].

2 DOSAGE AND ADMINISTRATION

The recommended dose of DUAKLIR PRESSAIR is one oral inhalation of 400 mcg/12 mcg, twice daily (once in the morning and once in the evening). Do not take more than one inhalation twice daily.

3 DOSAGE FORMS AND STRENGTHS

Inhalation Powder. DUAKLIR PRESSAIR is a breath-actuated multi-dose dry powder inhaler metering 400 mcg of aclidinium bromide and 12 mcg of formoterol fumarate per actuation.

4 CONTRAINDICATIONS

Use of a long-acting beta2-adrenergic agonist (LABA), including formoterol fumarate, one of the active ingredients in DUAKLIR PRESSAIR, without an inhaled corticosteroid is contraindicated in patients with asthma [see Warnings and Precautions (5.1)]. DUAKLIR PRESSAIR is not indicated for the treatment of asthma.

DUAKLIR PRESSAIR is contraindicated in patients with:

- Severe hypersensitivity to milk proteins [see Warnings and Precautions (5.5)].
- Hypersensitivity to aclidinium bromide, formoterol fumarate, or to any component of the product [see Warnings and Precautions (5.5)].

5 WARNINGS AND PRECAUTIONS

5.1 Serious Asthma-Related Events-Hospitalizations, Intubations, Death

- The safety and efficacy of DUAKLIR PRESSAIR in patients with asthma have not been established. DUAKLIR PRESSAIR is not indicated for the treatment of asthma. [see Contraindications (4)].
- Use of LABA as monotherapy [without inhaled corticosteroids (ICS)] for asthma is associated with an increased risk of asthma-related death. Available data from controlled clinical trials also suggest that use of LABA as monotherapy increases the risk of asthma-related hospitalization in pediatric and adolescent patients. These findings are considered a class effect of LABA monotherapy. When LABA are used in fixed-dose combination with ICS, data from large clinical trials do not show a significant increase in the risk of serious asthma-related events (hospitalizations, intubations, death) compared with ICS alone.
- A 28-week, placebo-controlled, U.S. trial comparing the safety of another LABA (salmeterol) with placebo, each added to usual asthma therapy, showed an increase in asthma-related deaths in subjects receiving salmeterol (13/13,176 in subjects treated with salmeterol vs 3/13,179 in subjects treated with placebo; relative risk: 4.37 [95% CI: 1.25, 15.34]). The increased risk of asthma-related death is considered a class effect of LABAs, including formoterol fumarate, one of the active ingredients in DUAKLIR PRESSAIR.
- No trial adequate to determine whether the rate of asthma-related deaths is increased in subjects treated with DUAKLIR PRESSAIR has been conducted.
- Available data do not suggest an increased risk of death with use of LABA in patients with COPD.

5.2 Deterioration of Disease and Acute Episodes

DUAKLIR PRESSAIR should not be initiated in patients with acutely deteriorating COPD, which may be a life-threatening condition. DUAKLIR PRESSAIR has not been studied in patients with acutely deteriorating COPD. The use of DUAKLIR PRESSAIR in this setting is inappropriate.

DUAKLIR PRESSAIR is intended as twice daily maintenance treatment for COPD and should not be used for the relief of acute symptoms, i.e., as rescue therapy for treatment of acute episodes of bronchospasm. DUAKLIR PRESSAIR has not been studied in the relief of acute symptoms and extra doses should not be used for that purpose. Acute symptoms should be treated with an inhaled short-acting beta2-agonist.

When beginning treatment with DUAKLIR PRESSAIR, patients who have been taking oral or inhaled, short-acting beta2-agonists on a regular basis (e.g., four times a day) should be instructed to discontinue the regular use of these drugs and use them only for symptomatic relief of acute respiratory symptoms. When prescribing DUAKLIR PRESSAIR, the healthcare provider should also prescribe an inhaled, short-acting beta2-agonist and instruct the patient on how it should be used. Increasing inhaled beta2-agonist use is a signal of deteriorating disease for which prompt medical attention is indicated.

COPD may deteriorate acutely over a period of hours or chronically over several days or longer. If DUAKLIR PRESSAIR no longer controls symptoms of bronchoconstriction; the patient’s inhaled, short-acting beta2-agonist becomes less effective; or the patient needs more short-acting beta2-agonist than usual, these may be markers of deterioration of disease. In this setting, a re-evaluation of the patient and the COPD treatment regimen should be undertaken at once. Increasing the daily dose of DUAKLIR PRESSAIR beyond the recommended dose is not appropriate in this situation.

5.3 Excessive Use of DUAKLIR PRESSAIR and Use with Other Long-Acting Beta2 Agonists

As with other inhaled drugs containing beta-agonists, DUAKLIR PRESSAIR should not be used more often than recommended, at higher doses than recommended, or in conjunction with other medications containing LABAs, as an overdose may result. Clinically significant cardiovascular effects and fatalities have been reported in association with excessive use of inhaled sympathomimetic drugs. Patients using DUAKLIR PRESSAIR should not use another medicine containing a LABA for any reason [see Drug Interactions (7.1)].

5.4 Paradoxical Bronchospasm

Inhaled medicines, including DUAKLIR PRESSAIR, may cause paradoxical bronchospasm, which may be life threatening. If paradoxical bronchospasm occurs following dosing with DUAKLIR PRESSAIR, it should be treated immediately with an inhaled, short acting bronchodilator. DUAKLIR PRESSAIR should be discontinued immediately, and alternative therapies should be instituted.

5.5 Immediate Hypersensitivity Reactions

Immediate hypersensitivity reactions including anaphylaxis, angioedema (including swelling of the lips, tongue, or throat), urticaria, rash, bronchospasm, or itching, have occurred after administration of DUAKLIR PRESSAIR. If such a reaction occurs, therapy with DUAKLIR PRESSAIR should be stopped at once and alternative treatments should be considered.

5.6 Cardiovascular Effects

Formoterol fumarate, like other beta agonists, can produce a clinically significant cardiovascular effect in some patients as measured by increases in pulse rate, systolic or diastolic or blood pressure, or symptoms [see Clinical Pharmacology (12.2)]. If such effects occur, DUAKLIR PRESSAIR may need to be discontinued.

In addition, beta-agonists have been reported to produce ECG changes, such as flattening of the T wave, prolongation of the QTc interval, and ST segment depression, although the clinical significance of these findings is unknown. Therefore, DUAKLIR PRESSAIR should be used with caution in patients with severe cardiovascular disorders, especially coronary insufficiency, cardiac arrhythmias, and hypertension.

5.7 Coexisting Conditions

DUAKLIR PRESSAIR, like other medications containing sympathomimetic amines, should be used with caution in patients with convulsive disorders, thyrotoxicosis, and in those who are unusually responsive to sympathomimetic amines. Doses of the related beta-agonist albuterol, when administered intravenously, have been reported to aggravate pre-existing diabetes mellitus and ketoacidosis.

5.8 Hypokalemia and Hyperglycemia

Beta-agonist medications may produce significant hypokalemia in some patients, possibly through intracellular shunting, which has the potential to produce adverse cardiovascular effects [see Clinical Pharmacology (12.2)]. The decrease in serum potassium is usually transient, not requiring supplementation. Beta-agonist medications may produce transient hyperglycemia in some patients. In 4 clinical trials of 24 to 52 weeks duration evaluating DUAKLIR PRESSAIR in patients with COPD, there was no evidence of a treatment effect on serum glucose or potassium.

5.9 Worsening of Narrow-Angle Glaucoma

DUAKLIR PRESSAIR should be used with caution in patients with narrow-angle glaucoma. Prescribers and patients should be alert for signs and symptoms of acute narrow-angle glaucoma (e.g., eye pain or discomfort, blurred vision, visual halos, or colored images in association with red eyes from conjunctival congestion and corneal edema). Instruct patients to consult a physician immediately should any of these signs or symptoms develop.

5.10 Worsening of Urinary Retention

DUAKLIR PRESSAIR should be used with caution in patients with urinary retention or bladder neck obstruction. Prescribers and patients should be alert for signs and symptoms of urinary retention (e.g., difficulty passing urine, painful urination), especially in patients with prostatic hyperplasia or bladder neck obstruction. Instruct patients to consult a physician immediately should any of these signs or symptoms develop.

6 ADVERSE REACTIONS

LABAs, such as formoterol fumarate, one of the active ingredients in DUAKLIR PRESSAIR, increase the risk of asthma-related death. DUAKLIR PRESSAIR is not indicated for the treatment of asthma [see Warnings and Precautions (5.1)].

The following adverse reactions are described in greater detail elsewhere in the labeling:

- Paradoxical bronchospasm [see Warnings and Precautions (5.4)]
- Immediate hypersensitivity reactions [see Contraindications (4), Warnings and Precautions (5.5)]
- Cardiovascular effects [see Warnings and Precautions (5.6)]
- Worsening of narrow-angle glaucoma [see Warnings and Precautions (5.9)]
- Worsening of urinary retention [see Warnings and Precautions (5.10)]

6.1 Clinical Trials Experience

Because clinical trials are conducted under widely varying conditions, adverse reaction rates observed in the clinical trials of a drug cannot be directly compared with rates in the clinical trials of another drug and may not reflect the rates observed in practice.

The clinical program for DUAKLIR PRESSAIR included 6501 subjects with COPD in 2 placebo-controlled and 1 active-controlled 24-week lung function trials, one long-term safety extension study of 28 weeks and 2 other clinical trials. A total of 1893 subjects have received at least 1 dose of DUAKLIR PRESSAIR.

24-Week Trials

The frequency of common adverse reactions in Table 1 below is based upon pooled data from two, double-blind, placebo-controlled parallel group clinical trials (Trials 1 and 2, n=1729 and n=1669) in 3398 adult patients with moderate to severe COPD. Of these, 60% were male and 94% were Caucasian. They had a mean age of 64 years and an average smoking history of 46 pack-years, with 49% identified as current smokers. At screening, the mean post-bronchodilator percent predicted forced expiratory volume in 1 second (FEV1) was 54% (range: 28% to 80%) and the mean percent reversibility was 15% (range: -19% to 69%).

Table 1 shows all adverse reactions that occurred with a frequency of greater than or equal to 3% in the DUAKLIR PRESSAIR group in the two 24-week placebo-controlled trials where the rates in the DUAKLIR PRESSAIR group exceeded placebo.

Table 1: Adverse Reactions with DUAKLIR PRESSAIR ≥3% Incidence and More Common than with Placebo in Subjects with COPD
 | Treatment
Adverse Reactions; Preferred Term | DUAKLIR PRESSAIR; (N=720); % | Aclidinium; (N=722); % | Formoterol; (N=716); % | Placebo; (N=526); %
Upper respiratory tract infection [Includes Viral Upper Respiratory Tract Infection and Upper Respiratory Tract Infection] | 8.9 | 7.6 | 8.9 | 6.3
Headache | 6.3 | 6.6 | 7.7 | 5.1
Back pain | 3.8 | 3.3 | 3.5 | 3.4

Other adverse reactions reported in clinical studies with an incidence of >1% but less than 3% with DUAKLIR PRESSAIR but more common than with placebo were cough, sinusitis, influenza, tooth abscess, insomnia, dizziness, dry mouth, oropharyngeal pain, muscle spasms, musculoskeletal pain, arthralgia, pain in extremity, urinary tract infection, and blood creatine phosphokinase increased.

The adverse events reported in the 24-week active-controlled trial were consistent with those observed in 24-week placebo-controlled trials.

Long-Term Safety Extension Trial

In a 28-week safety extension trial, 918 subjects who successfully completed Trial 2 were treated for up to an additional 28 weeks for a total treatment period of up to 52 weeks with DUAKLIR PRESSAIR, aclidinium 400 mcg, formoterol fumarate 12 mcg administered twice daily or placebo. Because the subjects continued from Trial 2 into the safety extension trial, the demographic and baseline characteristics of the long-term safety extension trial were similar to those of the placebo-controlled efficacy trials described above. The adverse reactions reported in the long-term safety trial were consistent with those observed in the 24-week placebo-controlled trials.

7 DRUG INTERACTIONS

No formal drug interaction studies have been performed with DUAKLIR PRESSAIR.

7.1 Adrenergic Drugs

If additional adrenergic drugs are to be administered by any route, they should be used with caution because the sympathetic effects of formoterol, a component of DUAKLIR PRESSAIR, may be potentiated [see Warnings and Precautions (5.7)].

7.2 Xanthine Derivatives, Steroids

Concomitant treatment with xanthine derivatives, or steroids may potentiate any hypokalemic effect of beta-adrenergic agonists such as formoterol, a component of DUAKLIR PRESSAIR.

7.3 Non-Potassium Sparing Diuretics

The electrocardiographic changes and/or hypokalemia that may result from the administration of non-potassium-sparing diuretics (such as loop or thiazide diuretics) can be acutely worsened by beta-agonists, especially when the recommended dose of the beta-agonist is exceeded. Although the clinical significance of these effects is not known, caution is advised in the coadministration of beta-agonists with non–potassium-sparing diuretics.

7.4 Monoamine Oxidase Inhibitors and Tricyclic Antidepressants, QTc Prolonging Drugs

DUAKLIR PRESSAIR, as with other drugs containing beta2-agonists, should be administered with caution to patients being treated with monoamine oxidase inhibitors, tricyclic antidepressants, or other drugs known to prolong the QTc interval, because the action of adrenergic agonists on the cardiovascular system may be potentiated by these agents. Drugs that are known to prolong the QTc interval have an increased risk of ventricular arrhythmias.

7.5 Beta-Blockers

Beta-adrenergic receptor antagonists (beta-blockers) and DUAKLIR PRESSAIR may inhibit the effect of each other when administered concurrently. Beta-blockers not only block the therapeutic effects of beta2-agonists, such as formoterol, a component of DUAKLIR PRESSAIR, but may produce severe bronchospasm in COPD patients. Therefore, patients with COPD should not normally be treated with beta-blockers. However, under certain circumstances, e.g., as prophylaxis after myocardial infarction, there may be no acceptable alternatives to the use of beta-blockers in patients with COPD. In this setting, cardioselective beta-blockers could be considered, although they should be administered with caution.

7.6 Anticholinergics

There is a potential for an additive interaction with concomitantly used anticholinergic medications. Therefore, avoid coadministration of DUAKLIR PRESSAIR with other anticholinergic-containing drugs as this may lead to an increase in anticholinergic effects [see Warnings and Precautions (5.3, 5.4) and Adverse Reactions (6)].

8 USE IN SPECIFIC POPULATIONS

8.1 Pregnancy

Risk Summary

There are no adequate and well-controlled studies of DUAKLIR PRESSAIR or its individual components, formoterol fumarate or aclidinium bromide, in pregnant women to inform drug-associated risks.

No adverse developmental effects were seen with inhalation administration of aclidinium bromide to pregnant rats and rabbits during organogenesis at 15 or 20 times, respectively, the maximum recommended human daily inhaled dose (MRHDID). However, reduced pup weights were seen when pregnant rats continued inhalation administration through lactation at 5 times the MRHDID of aclidinium bromide. Adverse developmental effects occurred when rabbits were orally dosed with aclidinium bromide at approximately 1,400 times the MRHDID [see Data].

Formoterol fumarate alone, administered by the oral route, was teratogenic in rats and rabbits at 1,200 and 49,000 times the MRHDID, respectively. Formoterol fumarate was also embryocidal, increased pup loss at birth and during lactation, and decreased pup weight in rats at 85 times the MRHDID. These adverse effects generally occurred at large multiples of the MRHDID when formoterol fumarate was administered by the oral route to achieve high systemic exposures. No teratogenic, embryocidal, or developmental effects were seen in rats that received inhalation doses up to 280 times the MRHDID [see Data].

The estimated background risk of major birth defects and miscarriage of the indicated populations is unknown. In the U.S. general population, the estimated background risk of major birth defects and miscarriage in clinically recognized pregnancies is 2% to 4% and 15% to 20%, respectively.

Clinical Considerations

Labor or Delivery

There are no well-controlled human studies that have investigated the effects of DUAKLIR PRESSAIR during labor and delivery. Because of the potential for beta-agonist interference with uterine contractility, use of DUAKLIR PRESSAIR during labor should be restricted to those patients in whom the benefits clearly outweigh the risk.

Data

Animal Data

Aclidinium bromide

In an embryo-fetal development study in pregnant rats dosed during the period of organogenesis from gestation days 6-17, no evidence of structural alterations was observed at approximately 15 times the maximum recommended human daily inhaled dose (MRHDID) [based on summed AUCs of aclidinium bromide and its metabolites at inhaled doses less than or equal to 5.0 mg/kg/day]. However, in a pre- and post-natal development study, decreased pup weights were observed when pregnant rats were exposed from gestation day 6 and continuing during the lactation period at approximately 5 times the MRHDID [based on summed AUCs of aclidinium bromide and its metabolites at inhaled doses greater than or equal to 0.2 mg/kg/day]. Maternal toxicity was also observed at inhaled doses greater than or equal to 0.2 mg/kg/day.

In an embryo-fetal development study in pregnant Himalayan rabbits administered inhaled doses of aclidinium bromide during the period of organogenesis from gestation days 6-19, no evidence of structural alterations was observed at approximately 20 times the MRHDID [based on summed AUCs of aclidinium bromide and its metabolites at inhaled doses less than or equal to 3.6 mg/kg/day]. However, in another embryo-fetal development study in pregnant Himalayan rabbits dosed orally from gestation days 6-19, increased incidences of additional liver lobes (3-5%), as compared to 0% in the control group, were observed at approximately 1,400 times the MRHDID [based on summed AUCs of aclidinium bromide and its metabolites at oral doses greater than or equal to 150 mg/kg/day], and decreased fetal body weights were observed at approximately 2,300 times the MRHDID [based on summed AUCs of aclidinium bromide and its metabolites at oral doses greater than or equal to 300 mg/kg/day]. These fetal findings were observed in the presence of maternal toxicity.

Formoterol fumarate

In a fertility and reproduction study, male rats were orally dosed for 9 weeks and females for 2 weeks prior to pairing and throughout the mating period. Females were either dosed up to gestation day 19 or up until weaning of their offspring. Males were dosed up to 25 weeks. Umbilical hernia was observed in rat fetuses at oral doses 1,200 times and greater than the MRHDID (on a mg/m^2 basis at maternal oral doses of 3 mg/kg/day and higher). Brachygnathia, abnormal shortness of the mandible, was observed in rat fetuses at a dose 6,000 times the MRHDID (on a mg/m^2 basis at a maternal oral dose of 15 mg/kg/day). Pregnancy was prolonged at a dose 6,000 times the MRHDID (on a mg/m^2 basis at a maternal oral dose of 15 mg/kg/day). Fetal and pup deaths occurred at doses approximately 1,200 times the MRHDID and higher (on a mg/m^2 basis at oral doses of 3 mg/kg/day and higher) during gestation.

In an embryo-fetal development study in pregnant rats dosed during the period of organogenesis from gestation days 6-15, no teratogenic, embryocidal or developmental effects were seen at doses up to 280 times the MRHDID (on a mg/m^2 basis with maternal inhalation doses up to 0.69 mg/kg/day).

In an embryo-fetal development study in pregnant rabbits dosed during the period of organogenesis from gestation days 6-18, subcapsular cysts on the liver were observed in the fetuses at a dose 49,000 times the MRHDID (on a mg/m^2 basis with a maternal oral dose of 60 mg/kg/day). No teratogenic effects were observed at doses up to 2,800 times the MRHDID (on a mg/m^2 basis at maternal oral doses up to 3.5 mg/kg/day).

In a pre- and post-natal development study, pregnant female rats received formoterol at oral doses of 0, 0.21, 0.84, and 3.4 mg/kg/day from gestation day 6 through the lactation period. Pup survival was decreased from birth to postpartum day 26 at doses 85 times the MRHDID and higher (on a mg/m^2 basis at maternal oral doses of 0.21 mg/kg/day and higher), although there was no evidence of a dose-response relationship. There were no treatment-related effects on the physical, functional, and behavioral development of rat pups.

8.2 Lactation

Risk Summary

There are no available data on the effects of DUAKLIR PRESSAIR, aclidinium bromide, or formoterol fumarate on the breastfed child or on milk production or presence in human milk. Both aclidinium bromide and formoterol fumarate are present in rat milk [see Data]. When a drug is present in animal milk, it is likely that the drug will be present in human milk. The developmental and health benefits of breastfeeding should be considered along with the mother’s clinical need for DUAKLIR PRESSAIR and any potential adverse effects on the breastfed child from DUAKLIR PRESSAIR or from the underlying maternal condition.

Data

In a pharmacokinetic study, levels of radioactivity in milk and plasma in rats were measured after a single intravenous dose of 1 mg/kg of radiolabeled aclidinium bromide on approximately post-natal day 14 [see Use in Specific Populations (8.1)]. The maximum concentration of radioactivity [^14C aclidinium] in milk was measured at 6 hours post-dose and was found to be 10-14 times higher than in plasma.

In the fertility and reproduction study in rats, plasma levels of formoterol were measured in pups on post-natal day 15 [see Use in Specific Populations (8.1)]. It was estimated that the maximum plasma concentration that the pups received from the maternal animal, at the highest dose of 15 mg/kg, after nursing was 4.4% (0.24 nmol/L for a litter vs. 5.5 nmol/L for the mother).

8.4 Pediatric Use

DUAKLIR PRESSAIR is not indicated for use in children. The safety and effectiveness of DUAKLIR PRESSAIR in the pediatric population have not been established.

8.5 Geriatric Use

Based on available data for DUAKLIR PRESSAIR or its active components, no adjustment of dosage in geriatric patients is warranted [see Clinical Pharmacology (12.3)].

Of the 720 COPD patients exposed to DUAKLIR PRESSAIR for 24 weeks in two placebo-controlled clinical trials, 238 were less than 60 years, 301 were greater than or equal to 60 to less than 70 years, and 181 were greater than or equal to 70 years of age.

No overall differences in safety or effectiveness were observed between these subjects and younger subjects. Other reported clinical experience has not identified differences in responses between the elderly and younger patients, but greater sensitivity of some older individuals cannot be ruled out.

8.6 Hepatic Impairment

Formal pharmacokinetic studies using DUAKLIR PRESSAIR have not been conducted in patients with hepatic impairment. Based on available data for aclidinium and formoterol, no adjustment of dosage in hepatically impaired subjects is warranted.

8.7 Renal Impairment

Formal pharmacokinetic studies using DUAKLIR PRESSAIR have not been conducted in patients with renal impairment. Based on available data for aclidinium and formoterol, no adjustment of dosage in renally impaired subjects is warranted.

10 OVERDOSAGE

DUAKLIR PRESSAIR contains both aclidinium and formoterol fumarate; therefore, the risks associated with overdosage for the individual components described below apply to DUAKLIR PRESSAIR. The most common symptoms are blurred vision, dry mouth, nausea, muscle spasms, tremor, headache, palpitations, and systolic hypertension.

Treatment of overdosage consists of discontinuation of DUAKLIR PRESSAIR together with institution of appropriate symptomatic and/or supportive therapy.

11 DESCRIPTION

DUAKLIR PRESSAIR consists of a dry powder formulation of aclidinium bromide and formoterol fumarate for oral inhalation only.

Aclidinium bromide, is an anticholinergic with specificity for muscarinic receptors. Aclidinium bromide is a synthetic, quaternary ammonium compound, chemically described as 1-azoniabicyclo[2.2.2]octane, 3-[(hydroxydi-2-thienylacetyl)oxy]-1-(3-phenoxypropyl)-, bromide, (3R)-. The structural formula is:

Aclidinium bromide is a white powder with a molecular formula of C26H30 NO4S2Br and a molecular mass of 564.56. It is very slightly soluble in water and ethanol and sparingly soluble in methanol.

Formoterol fumarate, a racemate, is a selective beta2-adrenergic agonist. Its chemical name is (±)-2-hydroxy-5-[(1RS)-1-hydroxy-2-[[(1RS)-2-(4-methoxyphenyl)-1methylethyl]-amino]ethyl]formanilide fumarate dihydrate. The structural formula is:

Formoterol fumarate (as a dihydrate) has a molecular weight of 840.91, and its molecular formula is (C19H24N2O4)2• C4H4O4•2H2O. Formoterol fumarate is a white to yellowish crystalline powder, which is freely soluble in glacial acetic acid, soluble in methanol, sparingly soluble in ethanol and isopropanol, slightly soluble in water, and practically insoluble in acetone, ethyl acetate, and diethyl ether.

DUAKLIR PRESSAIR is a breath-actuated multi-dose dry powder inhaler. Each actuation of DUAKLIR PRESSAIR provides a metered dose of 12 mg of the formulation which contains lactose monohydrate (which may contain milk proteins) as the carrier, 400 mcg of aclidinium bromide (equivalent to 343 mcg of aclidinium), and 12.0 mcg of formoterol fumarate (as a dihydrate, equivalent to 11.5 mcg of formoterol fumarate anhydrous and 9.8 mcg of formoterol). This results in delivery of 396 mcg of aclidinium bromide (equivalent to 340 mcg of aclidinium) and 11.8 mcg of formoterol fumarate (as a dihydrate, equivalent to 11.3 mcg of formoterol fumarate anhydrous and 9.7 mcg of formoterol) from the mouthpiece, based on in vitro testing at an average flow rate of approximately 63 L/min with constant volume of 2 L. The amount of drug delivered to the lungs will vary depending on patient factors such as inspiratory flow rate and inspiratory time.

12 CLINICAL PHARMACOLOGY

12.1 Mechanism of Action

DUAKLIR PRESSAIR

DUAKLIR PRESSAIR contains two bronchodilators: aclidinium a long-acting muscarinic antagonist (also known as an anticholinergic) and formoterol a long-acting beta2-adrenergic agonist. Further information regarding these two substances is provided below. The mechanism of action described below for the individual components apply to DUAKLIR PRESSAIR. These drugs represent two different classes of medications (a long-acting antimuscarinic agent and a selective long-acting beta2-adrenergic receptor agonist) that have different effects on clinical and physiological indices of COPD.

Aclidinium bromide

Aclidinium bromide is a long-acting antimuscarinic agent, which is often referred to as an anticholinergic. It has similar affinity to the subtypes of muscarinic receptors M1 to M5. In the airways, it exhibits pharmacological effects through inhibition of M3 receptors at the smooth muscle leading to bronchodilation. The competitive and reversible nature of antagonism was shown with human and animal origin receptors and isolated organ preparations. In preclinical in vitro as well as in vivo studies, prevention of acetylcholine-induced bronchoconstriction effects was dose-dependent and lasted longer than 24 hours. The clinical relevance of these findings is unknown. The bronchodilation following inhalation of aclidinium bromide is predominantly a site-specific effect.

Formoterol fumarate

Formoterol fumarate is a long-acting selective beta2-adrenergic receptor agonist (LABA) (beta2-agonist). Inhaled formoterol fumarate acts locally in the lung as a bronchodilator. In-vitro studies have shown that formoterol has more than 200-fold greater agonist activity at beta2-receptors than at beta1-receptors. The in-vitro binding selectivity to beta2-over beta1-adrenoceptors is higher for formoterol than for albuterol (5 times), whereas salmeterol has a higher (3 times) beta‑selectivity ratio than formoterol.

Although beta2-receptors are the predominant adrenergic receptors in bronchial smooth muscle and beta1-receptors are the predominant receptors in the heart, there are also beta2-receptors in the human heart comprising 10% to 50% of the total beta-adrenergic receptors. The precise function of these receptors has not been established, but they raise the possibility that even highly selective beta2-agonists may have cardiac effects.

The pharmacologic effects of beta2-adrenoceptor agonist drugs, including formoterol, are at least in part attributable to stimulation of intracellular adenyl cyclase, the enzyme that catalyzes the conversion of adenosine triphosphate (ATP) to cyclic-3', 5'-adenosine monophosphate (cyclic AMP). Increased cyclic AMP levels cause relaxation of bronchial smooth muscle and inhibition of release of mediators of immediate hypersensitivity from cells, especially from mast cells.

In vitro tests show that formoterol is an inhibitor of the release of mast cell mediators, such as histamine and leukotrienes, from the human lung. Formoterol also inhibits histamine-induced plasma albumin extravasation in anesthetized guinea pigs and inhibits allergen-induced eosinophil influx in dogs with airway hyper responsiveness. The relevance of these in vitro and animal findings to humans is unknown.

12.2 Pharmacodynamics

Cardiovascular effects

DUAKLIR PRESSAIR

The effect of DUAKLIR PRESSAIR on cardiac rhythm was assessed in a subset of subjects using 24-hour Holter monitoring in the 24-week placebo-controlled trials. The Holter monitoring population included 114 subjects on DUAKLIR PRESSAIR, 118 subjects on aclidinium bromide 400 mcg, 121 subjects on formoterol fumarate 12 mcg, and 81 subjects on placebo. No clinically meaningful effects on cardiac rhythm were observed.

12.3 Pharmacokinetics

Absorption

Following twice-daily oral inhalation administration of DUAKLIR PRESSAIR in COPD patients, mean maximum aclidinium and formoterol concentrations of 128 pg/mL and 17 pg/mL, respectively, occurred within 5 minutes after inhalation. Steady state was achieved within 5 days.

Distribution

Aclidinium: Aclidinium shows a volume of distribution of approximately 300 L following intravenous administration of 400 mcg in humans.

Formoterol: Over the concentration range of 10-500 nmol/L, plasma protein binding for the RR and SS enantiomers of formoterol was 46% and 58%, respectively. The concentrations of formoterol used to assess the plasma protein binding were higher than those achieved in plasma following inhalation of a single 54 mcg dose.

Elimination

Metabolism

Aclidinium: Clinical pharmacokinetics studies, including a mass balance study, indicate that the major route of metabolism of aclidinium is hydrolysis, which occurs both chemically and enzymatically by esterases.

Aclidinium is rapidly and extensively hydrolyzed in plasma to its alcohol and dithienylglycolic acid derivatives, neither of which binds to muscarinic receptors and are devoid of pharmacologic activity.

Therefore, due to the low plasma levels achieved at the clinically relevant doses, aclidinium and its metabolites are not expected to alter the disposition of drugs metabolized by the human CYP450 enzymes.

Formoterol:

Metabolism of formoterol is primarily by direct glucuronidation and by O-demethylation followed by conjugation to inactive metabolites. Secondary metabolic pathways include deformylation and sulfate conjugation. CYP2D6 and CYP2C have been identified as being primarily responsible for O-demethylation.

Excretion

Aclidinium: Total clearance was approximately 170 L/h after an intravenous dose of aclidinium bromide in young healthy volunteers with an inter-individual variability of 36%. Intravenously administered radiolabeled aclidinium bromide was administered to healthy volunteers and was extensively metabolized with 1% excreted as unchanged aclidinium. Approximately 54% to 65% of the radioactivity was excreted in urine and 20% to 33% of the dose was excreted in feces. The combined results indicated that almost the entire aclidinium bromide dose was eliminated by hydrolysis. After dry powder inhalation, urinary excretion of aclidinium is about 0.09% of the dose and the estimated effective half-life approximately 12 hours.

Formoterol: The excretion of formoterol was studied in four healthy subjects following simultaneous administration of radiolabeled formoterol via the oral and IV routes. In that study, 62% of the radiolabeled formoterol was excreted in the urine while 24% was eliminated in the feces.

Specific Populations

Geriatric Patients

The pharmacokinetic profile of aclidinium bromide and its main metabolites was assessed in 12 elderly COPD patients (aged 70 years or older) compared to a younger cohort of 12 COPD patients (40-59 years) that were administered 400 mcg aclidinium bromide once daily for 3 days via inhalation. No clinically significant differences in systemic exposure (AUC and Cmax) were observed when the two groups were compared. No dosage adjustment is necessary in elderly patients [see Use in Specific Populations (8.5)].

The pharmacokinetics of formoterol have not specifically been studied in geriatric patients.

Patients with Renal Impairment

The impact of renal disease upon the pharmacokinetics of aclidinium bromide was studied in 18 subjects with mild, moderate, or severe renal impairment. Systemic exposure (AUC and Cmax) to aclidinium and its main metabolites following single doses of 400 mcg aclidinium bromide was similar in renally impaired patients compared with 6 matched healthy control subjects. No dose adjustment is necessary in renally impaired patients [see Use in Specific Populations (8.6)]. Renal excretion of unchanged formoterol is low.

Patients with Hepatic Impairment

The effects of hepatic impairment on the pharmacokinetics of aclidinium bromide were not studied. However, hepatic insufficiency is not expected to have relevant influence on aclidinium bromide pharmacokinetics, since it is predominantly metabolized by chemical and enzymatic hydrolysis to products that do not bind to muscarinic receptors [see Use in Specific Populations (8.7)]. Specific data with formoterol is not available, but because formoterol is primarily eliminated via hepatic metabolism, an increased exposure can be expected in patients with severe liver impairment.

Drug Interactions Studies

Aclidinium: Formal drug interaction studies were not performed. In vitro studies using human liver microsomes indicated that aclidinium and its major metabolites do not inhibit CYP450, 1A2, 2A6, 2B6, 2C8, 2C9, 2C19, 2D6, 2E1, 3A4/5, or 4A9/11 at concentrations up to 1,000-fold higher than the maximum plasma concentration that would be expected to be achieved at the therapeutic dose. Therefore, it is unlikely that aclidinium causes CYP450 related drug interactions [see Drug Interactions (7)].

Formoterol: Specific drug-drug interaction studies with formoterol have not been performed.

13 NONCLINICAL TOXICOLOGY

13.1 Carcinogenesis, Mutagenesis, Impairment of Fertility

Studies in animals with the combination of aclidinium bromide and formoterol fumarate, to evaluate the potential for carcinogenesis, mutagenesis, or impairment of fertility, have not been performed. The data described below is from studies conducted on the individual components.

Aclidinium Bromide

Two-year inhalation studies were conducted in mice and rats to assess the carcinogenic potential of aclidinium bromide. No evidence of tumorigenicity was observed in rats and mice at aclidinium doses up to 0.20 and 2.4 mg/kg/day, respectively [approximately 10 and 80 times the Maximum Recommended Human Daily Inhalation Dose (MRHDID), respectively, based on summed AUCs of aclidinium bromide and its metabolites].

Aclidinium bromide was positive in the in vitro bacterial gene mutation assay and the in vitro thymidine locus mouse lymphoma assay. However, aclidinium bromide was negative in the in vivo mouse micronucleus assay and the in vivo/in vitro unscheduled DNA synthesis assay with rat liver.

Aclidinium bromide impaired several fertility and reproductive performance indices (increased number of days to mate, decreased conception rate, decreased number of corpora lutea, increased pre-implantation loss with consequent decreased number of implantations and live embryos) in both male and female rats administered inhaled doses greater than or equal to 0.8 mg/kg/day [approximately 15 times the MRHDID based on summed AUCs of aclidinium bromide and its metabolites]. These adverse fertility effects were observed in the presence of paternal toxicity as evidenced by mortality and decreased body weight gain. However, there were no effects on mating index and sperm number and morphology. In the separate fertility assessments (treated males mated with untreated females; treated females mated with untreated males), no effect was observed in male and female rats at inhaled doses of 1.9 and 0.8 mg/kg/day, respectively [approximately 30 and 15 times the MRHDID, respectively, based on summed AUCs of aclidinium bromide and its metabolites].

Formoterol Fumarate

Long-term studies were conducted in mice using oral administration and rats using inhalation administration to evaluate the carcinogenic potential of formoterol fumarate. In a 24-month carcinogenicity study in CD-1 mice, formoterol fumarate at oral doses of 0.1 mg/kg and above [approximately 20 times the maximum recommended human daily inhalation dose (MRHDID) on a mg/m^2 basis] caused a dose-related increase in the incidence of uterine leiomyomas.

In a 24-month carcinogenicity study in Sprague-Dawley rats, an increased incidence of mesovarian leiomyoma and uterine leiomyosarcoma were observed at the inhaled dose of 0.13 mg/kg (approximately 55 times the MRHDID on a mg/m^2 basis). No tumors were seen at 0.022 mg/kg (approximately 9 times the MRHDID on a mg/m^2 basis). Other beta-agonist drugs have similarly demonstrated increases in leiomyomas of the genital tract in female rodents. The relevance of these findings to human use is unknown.

Formoterol fumarate was not mutagenic or clastogenic in Ames Salmonella/microsome plate test, mouse lymphoma test, chromosome aberration test in human lymphocytes, and rat micronucleus test.

A reduction in fertility and/or reproductive performance was identified in male rats treated with formoterol at an oral dose of 15 mg/kg (approximately 6,000 times the MRHDID on a mg/m^2 basis). In a separate study with male rats treated with an oral dose of 15 mg/kg (approximately 6,000 times the MRHDID on a mg/m^2 basis), there were findings of testicular tubular atrophy and spermatic debris in the testes and oligospermia in the epididymides. No such effect was seen at 3 mg/kg (approximately 1,200 times the MRHDID on a mg/m^2 basis). No effect on fertility was detected in female rats at doses up to 15 mg/kg (approximately 6,000 times the MRHDID on a mg/m^2 basis).

14 CLINICAL STUDIES

The safety and efficacy of DUAKLIR PRESSAIR was evaluated in a clinical development program that included three dose ranging trials, one active and two placebo-controlled lung function trials of 24 weeks duration; and one 28-week long-term safety extension study. The efficacy of DUAKLIR was primarily based on one dose ranging trial in 128 subjects with COPD and the three 6-month duration confirmatory trials in 5015 subjects with COPD, including chronic bronchitis and emphysema.

14.1 Dose-Ranging Trials

Dose selection for DUAKLIR PRESSAIR for COPD was primarily based on data for the individual components, aclidinium bromide and formoterol fumarate, in COPD patients.

Aclidinium

Dose selection for aclidinium was supported by a 7-day, randomized, double-blind, active and placebo-controlled, crossover trial evaluating 3 doses of aclidinium bromide (400, 200, and 100 mcg) administered twice daily and an active control in 79 subjects with COPD. A dose ordering was observed, with the aclidinium bromide 400 mcg demonstrating larger improvements in FEV1 over 24 hours compared with aclidinium bromide 200 mcg and 100 mcg.

The change from baseline in FEV1 AUC0-12 from placebo after 7 days for the 100, 200, and 400 mcg doses were 154 mL (95% CI: 116, 192), 176 mL (95% CI: 137, 215), and 208 mL (95% CI: 170, 247), respectively. The results supported the selection of 400 mcg of aclidinium bromide twice daily in the confirmatory COPD trials.

Formoterol

Dose selection for formoterol was supported by a randomized, double-blind, placebo and active comparator (open-label) controlled, 5-period incomplete unbalanced crossover trial evaluating 3 doses of formoterol fumarate (24, 12, and 6 mcg) administered twice daily and an open-label active comparator in 132 subjects with COPD.

The change from baseline in FEV1 AUC0-12 from placebo after 7 days for the 6, 12, and 24 mcg doses were 108 mL (95% CI: 55, 161), 117 mL (95% CI: 64, 171), and 162 mL (95% CI: 107, 216), respectively. The results supported the evaluation of 12 mcg of formoterol twice daily in the confirmatory COPD trials.

14.2 Confirmatory Trials

The clinical development program for DUAKLIR PRESSAIR included two placebo-controlled [Trial 1 (NCT 01462942) and Trial 2 (NCT 01437397)] and one active-controlled [Trial 3 (NCT 02796677)] randomized, double-blind, parallel-group 24-week trials in subjects with moderate to very severe COPD, including chronic bronchitis and emphysema, designed to evaluate the efficacy of DUAKLIR PRESSAIR on lung function. The 24-week trials included 4,977 subjects >40 years of age that had a clinical diagnosis of COPD, with a smoking history greater than or equal to 10 pack-years, a post-albuterol FEV1 less than 80% of predicted normal values, and a ratio of FEV1/FVC of less than 0.7. The majority of these patients were male (61%) and Caucasian (94%) with a mean age of 64 years and an average smoking history of 46 pack-years (50% current smokers). During screening, mean post-bronchodilator percent predicted FEV1 was 53% (range: 10% to 86%) and mean percent reversibility was 15% (range: -33% to 121%).

Trials 1, 2, and 3 evaluated DUAKLIR PRESSAIR (aclidinium/formoterol fumarate) 400 mcg/12 mcg, aclidinium 400 mcg, and formoterol fumarate 12 mcg. Trials 1 and 2 included a placebo arm, and Trial 3 included an active, blinded, control arm.

The co-primary endpoints were change from baseline in trough FEV1 and change from baseline in one-hour post-dose FEV1 at Week 24 compared with formoterol fumarate 12 mcg and aclidinium 400 mcg, respectively.

In the three trials, DUAKLIR PRESSAIR demonstrated a statistically significant increase in mean change from baseline in trough FEV1 and change from baseline in one-hour post-dose FEV1 at Week 24 relative to formoterol fumarate 12 mcg and aclidinium 400 mcg, respectively (Table 2).

Table 2: Least Squares (LS) Mean Change from Baseline in 1-hour Morning Post dose FEV1 and Trough FEV1 at 24 weeks
 | 1-hour Post-dose FEV1 (L) |  | Trough FEV1 (L)
 | Difference from |  | Difference from
Treatment | Placebo [The placebo, aclidinium and formoterol fumarate comparators used the same inhaler and excipients as DUAKLIR PRESSAIR.]; (95% CI) | Aclidinium Bromide; 400 mcg; (95% CI) | Placebo; (95% CI) | Formoterol Fumarate; 12 mcg; (95% CI)
Trial 1
DUAKLIR PRESSAIR; 400 mcg/12 mcg; n=385 | n=194; 0.299 L; (0.255, 0.343) | n=383; 0.125 L; (0.090, 0.160) | n=194; 0.143 L; (0.101, 0.185) | n=383; 0.085 L; (0.051, 0.119)
Trial 2
DUAKLIR PRESSAIR; 400 mcg/12 mcg; n=335 | n=331; 0.284 L; (0.247, 0.320) | n=337; 0.108 L; (0.073, 0.144) | n=331; 0.130 L; (0.095, 0.165) | n=332; 0.045 L; (0.011, 0.079)
Trial 3
DUAKLIR PRESSAIR; 400 mcg/12 mcg; n=314 |  | n=475; 0.084 L; (0.051, 0.117) |  | n=319; 0.055 L; (0.023, 0.088)
n = Number in the intent to treat population

With the limited data available, there were consistent improvements in trough FEV1 and one-hour post-dose FEV1 with respect to age, sex, degree of airflow limitation, reversibility, GOLD stage, smoking status, or inhaled corticosteroid use.

In Trial 3, serial spirometric evaluations were performed throughout the 24-hour dosing interval in a subset of subjects (n=563) at Day 1 and Week 24. Results from Trial 3 are shown in Figures 1 and 2.

Figure 1: FEV1 profile for DUAKLIR PRESSAIR (AB/FF 400/12 mcg), aclidinium bromide 400 mcg, formoterol fumarate 12 mcg, over a 24-hour dosing interval at Day 1 (active control not shown)

Figure 2: FEV1 profile for DUAKLIR PRESSAIR (AB/FF 400/12 mcg), aclidinium bromide 400 mcg, formoterol fumarate 12 mcg, over a 24-hour dosing interval at Week 24 (active control not shown)

In Trials 1 and 2, DUAKLIR PRESSAIR displayed an increase in FEV1 compared to placebo of 0.108 L (95% CI; 0.089, 0.127) and 0.128 L (95% CI; 0.111, 0.145) within 5 minutes after the first dose, respectively.

In Trials 1 and 2, patients treated with DUAKLIR PRESSAIR used less rescue medication compared to patients treated with placebo.

The St. George’s Respiratory Questionnaire (SGRQ) was assessed in Trials 1, 2, and 3. In Trial 1, the SGRQ responder rate (defined as an improvement in score of 4 or more as threshold) was 55.3%, 53.5%, 52.1%, and 53.2% for DUAKLIR PRESSAIR, aclidinium, formoterol fumarate, and placebo, respectively, with odds ratios of 1.12 (95% CI: 0.76, 1.67) for DUAKLIR PRESSAIR vs. aclidinium, 1.16 (95% CI: 0.78, 1.73) for DUAKLIR PRESSAIR vs. formoterol fumarate, and 1.12 (95% CI: 0.68, 1.84) for DUAKLIR PRESSAIR vs. placebo. In Trial 2, the SGRQ responder rate was 58.2%, 54.5%, 52.4%, and 38.7% for DUAKLIR PRESSAIR, aclidinium, formoterol fumarate, and placebo, respectively, with odds ratios of 1.03 (95% CI: 0.66, 1.62), 1.21 (95% CI: 0.77, 1.90), and 2.26 (95% CI: 1.41, 3.61), for DUAKLIR PRESSAIR vs. aclidinium, DUAKLIR PRESSAIR vs. formoterol fumarate, and DUAKLIR PRESSAIR vs. placebo, respectively. In Trial 3, the odds ratios were 0.96 (95% CI: 0.61, 1.51) and 0.97 (95% CI: 0.59, 1.58), for DUAKLIR PRESSAIR vs. aclidinium, DUAKLIR PRESSAIR vs. formoterol fumarate, respectively.

Exacerbations

A randomized, double-blind, placebo-controlled study of up to 36 months evaluated the efficacy of aclidinium bromide 400 mcg on COPD exacerbations in patients with moderate to very severe COPD with and without a history of exacerbations. The trial enrolled 3630 COPD patients, aged between 40 and 91 years, 58.7% were male and 90.6% were Caucasian, with a mean post-bronchodilator FEV1 of 47.7% of predicted value. The majority of patients had moderate (45.1%) or severe (40.2%) airflow obstruction.

The primary efficacy endpoint was the rate of moderate to severe exacerbations during the first year of treatment, defined as worsening of COPD symptoms (dyspnea, cough, sputum) for at least 2 consecutive days that required treatment with antibiotics and/or systemic corticosteroids or resulted in hospitalization or lead to death. Aclidinium bromide demonstrated a statistically significant reduction in the rate of on-study moderate to severe COPD exacerbations by 17% compared to placebo (rate ratio [RR] 0.83; 95% CI 0.73 to 0.94; p=0.003).

16 HOW SUPPLIED/STORAGE AND HANDLING

DUAKLIR PRESSAIR 400 mcg/12 mcg (aclidinium bromide and formoterol fumarate inhalation powder) is supplied in a sealed bag with a desiccant sachet and is available in 60 metered doses (NDC 0310-0900-60) and 30 metered doses (NDC 0310-0900-30).

The active ingredients are administered using a multi-dose dry powder inhaler, PRESSAIR®, which delivers 60 doses or 30 doses of aclidinium bromide and formoterol fumarate powder for oral inhalation. The PRESSAIR inhaler is a white and orange colored device and is comprised of an assembled plastic dosing mechanism with a dose indicator, a drug-product storage unit containing the drug-product formulation, and a mouthpiece covered by an orange protective cap.

Store DUAKLIR PRESSAIR in a dry place at 20°C-25°C (68°F-77°F); excursions permitted to 15-30°C (59-86°F) [see USP Controlled Room Temperature]. Do not store the inhaler on a vibrating surface.

The PRESSAIR inhaler should be stored inside the sealed bag and only be opened immediately before use. Throw away the bag and the desiccant sachet.

Throw away (dispose of) the PRESSAIR inhaler after the marking “0” with a red background shows in the middle of the dose indicator, when the device is empty and locks out, or 2 months after the date you opened the sealed bag that the inhaler comes in, whichever comes first.

Keep out of reach of children.

17 PATIENT COUNSELING INFORMATION

See FDA-approved Patient Labeling (Patient Information and Instructions for Use)

- Serious Asthma-Related Events

Inform patients that LABAs, such as formoterol fumarate, one of the active ingredients in DUAKLIR PRESSAIR, when used alone (without an inhaled corticosteroid), increase the risk of serious asthma-related events, including asthma-related death. DUAKLIR PRESSAIR is not indicated for the treatment of asthma.

- Not for Acute Symptoms

DUAKLIR PRESSAIR is not meant to relieve acute symptoms of COPD and extra doses should not be used for that purpose.

Instruct patients to seek medical attention immediately if they experience a worsening of symptoms or a need for more inhalations of their rescue inhaler than usual.

Instruct patients not to stop therapy with DUAKLIR PRESSAIR without physician/provider guidance since symptoms may recur after discontinuation.

- Do Not Use Additional Long-Acting Beta2-Agonists

Instruct patients to not use other medicines containing a LABA. Patients should not use more than the recommended dose of DUAKLIR PRESSAIR.

Instruct patients who have been taking inhaled, short-acting beta-agonists on a regular basis to discontinue the regular use of these products and use them only for the symptomatic relief of acute symptoms.

- Paradoxical Bronchospasm

Inform patients that DUAKLIR PRESSAIR can cause paradoxical bronchospasm. Advise patients that if paradoxical bronchospasm occurs, patients should discontinue DUAKLIR PRESSAIR.

- Visual Effects

Eye pain or discomfort, blurred vision, visual halos, or colored images in association with red eyes from conjunctival congestion and corneal edema may be signs of acute narrow-angle glaucoma. Inform patients to consult a physician immediately should any of these signs and symptoms develop.

Inform patients that care must be taken not to allow the powder to enter into the eyes as this may cause blurring of vision and pupil dilation.

- Urinary Retention

Difficulty passing urine and dysuria may be symptoms of new or worsening prostatic hyperplasia or bladder outlet obstruction. Patients should be instructed to consult a physician immediately should any of these signs or symptoms develop.

- Immediate Hypersensitivity Reactions

Inform patients that anaphylaxis, angioedema (including swelling of the lips, tongue, or throat), urticaria, rash, bronchospasm, or itching, may occur after administration of DUAKLIR PRESSAIR. Advise patient to immediately discontinue treatment and consult a physician should any of these signs or symptoms develop.

- Risks Associated with Beta2-Agonist Therapy

Inform patients of adverse effects associated with beta2-agonists, such as palpitations, chest pain, rapid heart rate, tremor, or nervousness.

- Instructions for Administering DUAKLIR PRESSAIR

It is important for patients to understand how to correctly use DUAKLIR PRESSAIR. Instruct patients not to use more than the recommended dose of DUAKLIR PRESSAIR or with other medicines containing LABAs as excessive use may lead to significant cardiovascular effects including fatalities.

Inform patients that if they miss a dose, they should take their next dose at the usual time; they should not take 2 doses at one time.

Instruct patients to thoroughly read complete Instructions for Use before using DUAKLIR PRESSAIR.

Manufactured for:

Covis Pharma
Zug, 6300 Switzerland

Under license of ALMIRALL, S.A.

DUAKLIR®and the logo are registered trademarks of Almirall, S.A., used under license by Covis Pharma.

PRESSAIR®is a registered trademark of the AstraZeneca group of companies, used under license by Covis Pharma.

Patient Information

DUAKLIR™ PRESSAIR® (DU-aakl-ir PRESS-air)

(aclidinium bromide and formoterol fumarate)

inhalation powder, for oral Inhalation use

Important: Do not get DUAKLIR PRESSAIR in your eyes.

What is DUAKLIR PRESSAIR?

DUAKLIR PRESSAIR combines an anticholinergic, aclidinium bromide, and a long-acting beta2-adrenergic agonist (LABA medicine) formoterol fumarate.

- Anticholinergic and LABA medicines help the muscles around the airways in your lungs stay relaxed to prevent symptoms such as wheezing, cough, chest tightness, and shortness of breath. These symptoms can happen when the muscles around the airways tighten. This makes it hard to breathe.
- DUAKLIR PRESSAIR is a prescription medicine that is used to treat COPD. COPD is a chronic lung disease that includes chronic bronchitis, emphysema, or both.
- DUAKLIR PRESSAIR is used long term as 1 inhalation 2 times each day to improve symptoms of COPD for better breathing and to reduce the number of flare-ups (the worsening of your COPD symptoms for several days).
- DUAKLIR PRESSAIR is not for use to treat sudden symptoms of COPD. Always have a rescue inhaler (short-acting beta2 agonist medicine) with you to treat sudden symptoms of COPD. If you do not have a rescue inhaler, contact your healthcare provider to have one prescribed for you.
- DUAKLIR PRESSAIR is not for the treatment of asthma. It is not known if DUAKLIR PRESSAIR is safe and effective in people with asthma.
- DUAKLIR PRESSAIR should not be used in children. It is not known if DUAKLIR PRESSAIR is safe and effective in children.

Do not use DUAKLIR PRESSAIR if you:

- have asthma and you use DUAKLIR PRESSAIR without also using a medicine called an inhaled corticosteroid.
- have a severe allergy to milk proteins. Ask your healthcare provider if you are not sure.
- are allergic to aclidinium bromide, formoterol fumarate, or any of the ingredients in DUAKLIR PRESSAIR. See “What are the ingredients in DUAKLIR PRESSAIR?” below for a complete list of ingredients.

Before you use DUAKLIR PRESSAIR tell your healthcare provider about all of your medical conditions, including if you:

- have heart problems
- have high blood pressure
- have seizures
- have thyroid problems
- have diabetes
- have eye problems especially glaucoma. DUAKLIR PRESSAIR may make your glaucoma worse.
- have prostate or bladder problems, or problems passing urine. DUAKLIR PRESSAIR may make these problems worse.
- are pregnant or plan to become pregnant. It is not known if DUAKLIR PRESSAIR can harm your unborn baby.
- are breastfeeding or plan to breastfeed. It is not known if the medicines, aclidinium bromide and formoterol fumarate in DUAKLIR PRESSAIR pass into your breast milk and if they can harm your baby.

Tell your healthcare provider about all the medicines you take, including prescription and over-the-counter medicines, vitamins, and herbal supplements.

DUAKLIR PRESSAIR and certain other medicines may interact with each other. This may cause serious side effects.

Especially tell your healthcare provider if you take:

- anticholinergics (including umeclidinium, tiotropium, ipratropium, aclidinium, glycopyrrolate).
- other LABA medicines (including formoterol, arformoterol, salmeterol, vilanterol, indacaterol, olodaterol).
- atropine

Know the medicines you take. Keep a list of them to show your healthcare provider and pharmacist when you get a new medicine.

How should I use DUAKLIR PRESSAIR?

Read the step-by-step instructions for using DUAKLIR PRESSAIR at the end of this Patient Information.

- Do not use DUAKLIR PRESSAIR unless your healthcare provider has taught you how to use the inhaler and you understand how to use it correctly.
- Use DUAKLIR PRESSAIR exactly as prescribed. Do not use DUAKLIR PRESSAIR more often than prescribed.
- Use 1 inhalation 2 times each day. Use DUAKLIR PRESSAIR 1 time in the morning and 1 time in the evening.
- If you miss a dose of DUAKLIR PRESSAIR skip the missed dose. Take your next dose at your usual time. Do not take more than 1 inhalation 2 times each day. Do not take 2 doses at one time.
- If you take too much DUAKLIR PRESSAIR, call your healthcare provider and get medical help right away if you have any unusual symptoms, such as worsening shortness of breath, chest pain, increased heart rate, or shakiness.
- Do not use other medicines that contain a LABA for any reason. Ask your healthcare provider or pharmacist if any of your other medicines are LABA medicines.
- Do not stop using DUAKLIR PRESSAIR unless told to do so by your healthcare provider because your symptoms might get worse. Your healthcare provider will change your medicines as needed.
- DUAKLIR PRESSAIR does not relieve sudden symptoms. Always have a rescue inhaler with you to treat sudden symptoms. If you do not have a rescue inhaler, call your healthcare provider to have one prescribed for you.
- Call your healthcare provider or get medical care right away if your breathing problems get worse, you need to use your rescue inhaler more often than usual, your rescue inhaler does not work as well to relieve your symptoms.

What are the possible side effects of DUAKLIR PRESSAIR?

DUAKLIR PRESSAIR can cause serious side effects including:

- people with asthma who take LABA medicines, such as formoterol fumarate (one of the medicines in DUAKLIR PRESSAIR), without also using a medicine called an inhaled corticosteroid, have an increased risk of serious problems from asthma, including being hospitalized, needing a tube placed in their airway to help them breathe or death.
  - Call your healthcare provider if breathing problems worsen over time with using DUAKLIR PRESSAIR.
    You may need a different treatment.
  - Get emergency medical care if:
    - your breathing problems worsen quickly
    - you use your rescue inhaler, but it does not relieve your breathing problems

- COPD symptoms that get worse over time. If your COPD symptoms worsen over time, do not increase your dose of DUAKLIR PRESSAIR, call your healthcare provider.

- using too much of a LABA medicine may cause:
  - chest pain
  - fast and irregular heartbeat
  - tremor

- sudden breathing problems immediately after use of DUAKLIR PRESSAIR. These sudden breathing problems may be life-threatening. If you have sudden breathing problems immediately after inhaling DUAKLIR PRESSAIR, stop using DUAKLIR PRESSAIR and call your healthcare provider right away or go to the nearest hospital emergency room.
- serious allergic reactions. Call your doctor or get emergency medical care if you get any symptoms of a serious allergic reaction.

- rash
- hives

- swelling of the face, mouth and tongue
- breathing problems

- effects on your heart:

- chest pain
- increased blood pressure

- fast or irregular heartbeat

- changes in laboratory blood levels: high blood sugar (hyperglycemia) and low blood potassium (hypokalemia), this last may cause symptoms of muscle spasms, muscle weakness, or abnormal heart rhythm.
- new or worsened increased pressure in your eyes (acute narrow-angle glaucoma). Acute narrow-angle glaucoma can lead to permanent loss of vision if not treated. Symptoms of acute narrow-angle glaucoma may include:

- eye pain or discomfort
- seeing halos or bright colors around lights

- nausea or vomiting
- red eyes

- blurred vision

If you have these symptoms, stop using DUAKLIR PRESSAIR and call your healthcare provider right away.

- new or worsened urinary retention. Urinary retention can be caused by blockage in your bladder or, if you are a male, a larger than normal prostate. Symptoms of urinary retention may include:

- difficulty urinating
- painful urination

- urinating frequently
- urination in a weak stream or drips

If you have these symptoms of urinary retention, stop using DUAKLIR PRESSAIR and call your doctor right away.

The most common side effects of DUAKLIR PRESSAIR include: upper respiratory tract infection, headache and, back pain.

Tell your healthcare provider about any side effect that bothers you or does not go away.

These are not all the possible side effects of DUAKLIR PRESSAIR. For more information, ask your healthcare provider or pharmacist.

Call your doctor for medical advice about side effects. You may report side effects to FDA at 1-800-FDA-1088.

How should I store DUAKLIR PRESSAIR?

- Store DUAKLIR PRESSAIR at room temperature between 68°F to 77°F (20°C to 25°C) in the sealed bag that it comes in until you are ready to use DUAKLIR PRESSAIR. Do not open the sealed bag until you are ready to use a dose of DUAKLIR PRESSAIR.
- Keep DUAKLIR PRESSAIR in a dry place.
- Do not store the inhaler on a vibrating surface.
- Throw away (dispose of) DUAKLIR PRESSAIR® and use a new one:
  - when the marking “0” with a red background shows in the middle of the dose indicator,
  - if your inhaler is empty and locks out, or
  - 2 months after the date you opened the sealed bag that the inhaler comes in, whichever comes first.
Keep DUAKLIR PRESSAIR and all medicines out of the reach of children.

General information about the safe and effective use of DUAKLIR PRESSAIR

Medicines are sometimes prescribed for purposes other than those listed in a Patient Information leaflet. Do not use DUAKLIR PRESSAIR for a condition for which it was not prescribed. Do not give your DUAKLIR PRESSAIR to other people, even if they have the same symptoms that you have. It may harm them.

You can ask your doctor or pharmacist for information about DUAKLIR PRESSAIR that is written for healthcare professionals.

What are the ingredients in DUAKLIR PRESSAIR?

Active ingredient: aclidinium bromide and formoterol fumarate

Inactive ingredient: lactose monohydrate

Manufactured for: Covis Pharma, Zug, 6300 Switzerland

© Covis Pharma 2022

This Patient Information has been approved by the U.S. Food and Drug Administration
08/2022

PATIENT INFORMATION

Instructions for Use

DUAKLIR® PRESSAIR® (DU-aakl-ir PRESS-air)

(aclidinium bromide/formoterol fumarate) inhalation powder

For oral Inhalation only

This Instructions for Use contains information on how to use your DUAKLIR PRESSAIR inhaler. It is important that you read this information as the DUAKLIR PRESSAIR may work differently from inhalers you have used before.

Read this Instructions for Use before you start using DUAKLIR PRESSAIR and each time you get a refill. There may be new information. This information does not take the place of talking to your doctor about your medical condition or your treatment.

If you have any questions about how to use your inhaler, ask your doctor, pharmacist, or nurse for help.

The Instructions for Use is divided into the following sections:

- Getting started

- Before use

- Step 1: Prepare your dose

- Step 2: Inhale your medicine

- Additional information

- Questions and Answers about your DUAKLIR PRESSAIR inhaler

Getting Started

Become familiar with the parts of your DUAKLIR PRESSAIR inhaler (Figure A).

Before use:

1. Right before first use, open the sealed bag at the arrow marking and remove the inhaler. Throw away the bag and the desiccant.
2. Write the date that you open the sealed bag on the label of the inhaler.
3. Do not press the orange button until you are ready to take a dose.
4. Remove the protective cap by lightly squeezing the arrows marked on each side of the protective cap and pulling straight off (Figure B).

Step 1: Prepare your dose

1.1. Look in the opening of the mouthpiece and make sure nothing is blocking it (Figure C).

1.2. Look at the control window. The control window should be red (Figure C).

1.3. Hold the inhaler horizontally with the mouthpiece facing you and the orange button on top (Figure D).

1.4. Press the orange button all the way down to load your dose (Figure E).

When you press the orange button all the way down, the control window changes from red to green.

Make sure the orange button is on top. Do not tilt the inhaler.

1.5. Release the orange button (Figure F).

Make sure you release the orange button, so the inhaler can work correctly.

Stop and Check:

1.6. Make sure the control window is now green (Figure G).

This means your medicine is ready to be inhaled.

Go to “Step 2: Inhale your medicine”.

What to do if the control window is still red after pressing the button (Figure H).

The dose is not prepared. Go back to “Step 1 Prepare your dose” and repeat steps 1.1 to 1.6.

Step 2: Inhale your medicine

Read steps 2.1 to 2.7 fully before use. Do not tilt the inhaler.

2.1. Hold the inhaler away from your mouth, and breathe out completely. Never breathe out into the inhaler (Figure I).

2.2. Hold your head upright, put the mouthpiece between your lips, and close your lips tightly around the mouth piece (Figure J).

Do not hold the orange button down while inhaling

2.3. Take a strong, deep breath through your mouth. Keep breathing in for as long as possible.

A “click” will let you know that you are inhaling correctly. Keep breathing in as long as possible after you hear the “click”. Some people may not hear the “click”. Use the control window to make sure you have inhaled correctly.

2.4. Take the inhaler out of your mouth.

2.5. Hold your breath for as long as possible.

2.6. Slowly breathe out away from the inhaler.

Some people may have a grainy sensation in their mouth, or a slightly sweet or bitter taste. Do not take an extra dose if you do not taste or feel anything after inhaling.

Stop and Check:

2.7. Make sure the control window is now red (Figure K). This means you have inhaled your medicine correctly.

What to do if the control window is still green after inhalation (Figure L).

This means you have not inhaled your medicine correctly. Go back to “Step 2 Inhale your medicine” and repeat steps 2.1 to 2.7.

If the control window still does not change to red, you may have forgotten to release the orange button before inhaling, or you may not have inhaled strongly enough. If this happens, try again. Make sure you have released the orange button, and you have breathed out completely. Then take a strong, deep breath through the mouthpiece.

Contact your doctor if the control window is still green after repeated attempts.

Push the protective cap back onto the mouthpiece after each use (Figure M), to prevent contamination of the inhaler with dust or other materials. You should throw away (dispose of) your inhaler if you lose the protective cap.

Additional information

What should I do if I accidentally prepare a dose?

Store your inhaler with the protective cap in place until it is time to inhale your medicine, then remove the cap and start at Step 1.6.

How does the dose indicator work?

- The dose indicator shows the total number of doses left in the inhaler (Figure N).
- On first use, every inhaler contains at least 60 doses.
- Each time you load a dose by pressing the orange button, the dose indicator moves by a small amount towards the next number (50, 40, 30, 20, 10, or 0).

When should I get a new inhaler?

You should throw away (dispose of) your inhaler if it appears to be damaged or if you lose the protective cap.

When a red band appears in the dose indicator, this means you are close to your last dose (Figure N).

You should throw away (dispose of) the inhaler and use a new one:

- when the marking “0” with a red background shows in the middle of the dose indicator (Figure O), or
- if your inhaler is empty and locks out (Figure P), or
- two months after the date you opened the sealed bag that the inhaler comes in, whichever comes first.

How do I know that my inhaler is empty?

When the orange button will not return to its full upper position and is locked in a middle position (Figure P). Even though the orange button is locked, your last dose may still be inhaled. After that, the inhaler cannot be used again and you should start using a new inhaler.

How should I clean the inhaler?

Never use water to clean the inhaler, as this may damage your medicine.

If you want to clean your inhaler, wipe the outside of the mouthpiece with a dry tissue or paper towel.

How should I store DUAKLIR PRESSAIR?

- Store DUAKLIR PRESSAIR at room temperature between 68°F to 77°F (20°C to 25°C) in the sealed bag that it comes in until you are ready to use DUAKLIR PRESSAIR. Do not open the sealed bag until you are ready to use a dose of DUAKLIR PRESSAIR.
- Keep DUAKLIR PRESSAIR in a dry place.
- Do not store the inhaler on a vibrating surface.

Keep DUAKLIR PRESSAIR and all medicines out of the reach of children.

Questions and Answers about your DUAKLIR PRESSAIR Inhaler

Question

Answer

Do I need to take extra steps to prepare the inhaler before first use?

DUAKLIR PRESSAIR comes preloaded with medicine and is ready to use. Remove the inhaler from the sealed bag and follow the step-by-step Instructions for Use.

How do I know if the DUAKLIR PRESSAIR inhaler is ready to use before taking each dose?

The DUAKLIR PRESSAIR inhaler is ready to use when the control window on the front of the inhaler is green (Figure G)

- If the control window is red (see Step 1.6), press and release the orange button completely. This will change the color of the control window from red to green, indicating the medicine is ready to inhale.

What if the DUAKLIR PRESSAIR inhaler window doesn't change from red to green?

The dose is not prepared. Go back to “Step 1 Prepare your dose” and repeat steps 1.1 to 1.6.

- If the orange button is locked, you have used all the medicine in your inhaler and should get a new DUAKLIR PRESSAIR inhaler (Figure P).

How do I know that I used DUAKLIR PRESSAIR correctly?

The DUAKLIR PRESSAIR inhaler has a helpful feature to let you know that you have inhaled your medicine correctly.

- Look at the control window to see if it has turned to red after you have inhaled fully through the mouthpiece. If the control window is red you have inhaled your full dose of medicine correctly (see Step 2.7).

What if the DUAKLIR PRESSAIR inhaler control window does not change color from green back to red after I inhale?

This means you may not have inhaled the medicine strongly enough. Go back to “Step 2 Inhale your medicine” and repeat steps 2.1 to 2.7.

- Did you breathe out completely before inhaling?
- Did you let go of the orange button before inhaling?
- Did you form a tight seal with your lips around the mouthpiece?
- Did you breathe in strongly and deeply?
- Did you keep breathing in after you heard the “click”?

What if I do not see the dose indicator move after I inhaled?

Each time you load a dose by pressing the orange button, the dose indicator moves by a small amount towards the next number from 60 to 0: 60, 50, 40, 30, 20, 10, 0 (see Figure N). As long as you see the control window change from green to red, you have successfully inhaled the full dose.

Can the DUAKLIR PRESSAIR inhaler release too much medicine or lose doses of medicine from the inhaler?

No. The DUAKLIR PRESSAIR inhaler only releases 1 dose of medicine with each inhalation. Pressing and releasing the orange button more than one time before inhaling does not increase the dose you will receive or cause any medicine to be lost.

This Instructions for Use has been approved by the U.S. Food and Drug Administration.

Manufactured for:

Covis Pharma

Zug, 6300 Switzerland

Under license of ALMIRALL, S.A.

DUAKLIR® and the logo are registered trademarks of Almirall, S.A., used under license by Covis Pharma.

PRESSAIR® is a registered trademark of the AstraZeneca group of companies, used under license by Covis Pharma.

© 2022 Covis Pharma

Last revised: August 1, 2022

PRINCIPAL DISPLAY PANEL - 60 Metered Doses Carton

Carton - 60 Metered Doses

NDC 70515-001-01 Rx only

Duaklir® Pressair® 400 mcg/12 mcg
(aclidinium bromide and formoterol fumarate*) inhalation powder
400 mcg/12 mcg per actuation
For Oral Inhalation Only

*Each metered dose contains 400 mcg of aclidinium bromide
(equivalent to 343 mcg of aclidinium), and 12.0 mcg of formoterol
fumarate (as a dihydrate, equivalent to 9.8 mcg of formoterol)
from the device reservoir.

60 Metered Doses

COVIS